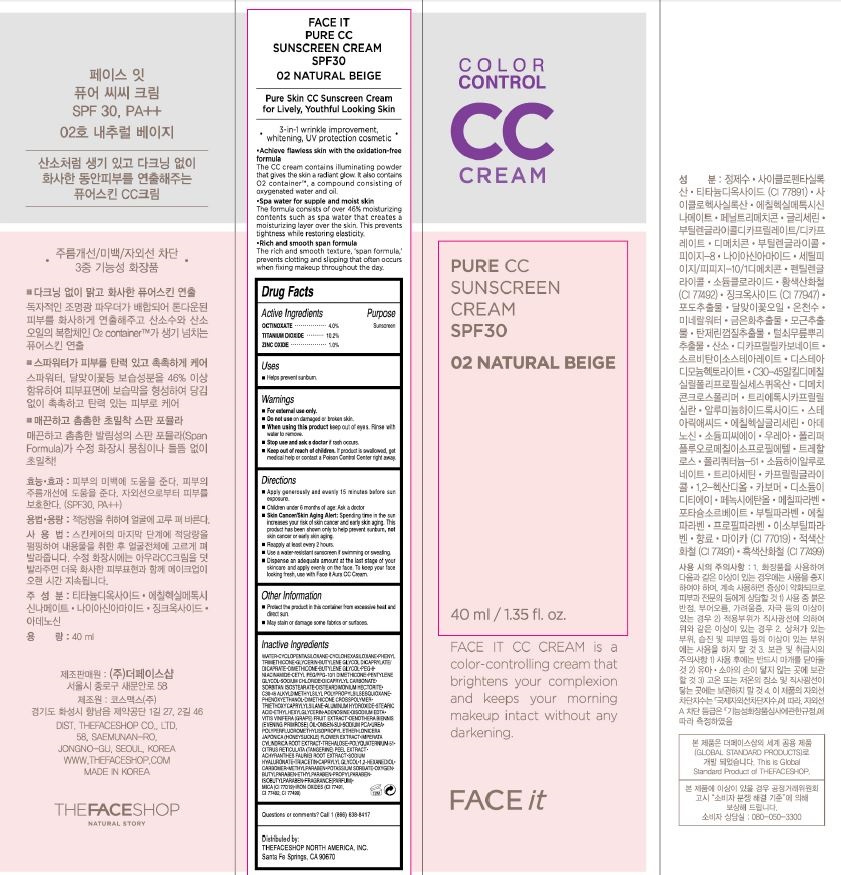 DRUG LABEL: FACET IT PURE COLOR CONTROL
NDC: 51523-851 | Form: CREAM
Manufacturer: THEFACESHOP CO., LTD.
Category: otc | Type: HUMAN OTC DRUG LABEL
Date: 20141120

ACTIVE INGREDIENTS: OCTINOXATE 1.6 g/40 mL; TITANIUM DIOXIDE 4.1 g/40 mL; ZINC OXIDE .4 g/40 mL
INACTIVE INGREDIENTS: WATER

Active Ingredients

OCTINOXATE 4.0%
TITANIUM DIOXIDE 10.2%,
ZINC OXIDE 1.0%

Purpose

Sunscreen

Sunscreen

Sunscreen

Warnings

For external use only.

Do not use on damaged or broken skin

When using this product keep out of eyes. Rinse with water to remove.

Stop use and ask a doctor if rash occurs.

Keep out of reach of children.

If product is swallowed, get medical help or contact a Poison Control Center right away.

Directions

Apply generously and evenly 15 minutes before
sun exposure.
Children under 6 months of age: Ask a doctor
Skin Cancer/Skin Aging Alert: Spending time in
the sun increases your risk of skin cancer and early
skin aging. This product has been shown only to
help prevent sunburn, not skin cancer or early skin
aging.
Reapply at least every 2 hours.
Use a water-resistant sunscreen if swimming or sweating.
Dispense an adequate amount at the last stage of
your skincare and apply evenly on the face.

To keep your face looking fresh, use with Face it Aura CC
Cream.

Other Information

Protect the product in this container from excessive heat and direct sun

May stain or damage some fabrics or surfaces

Inactive Ingredients

WATER•CYCLOPENTASILOXANE•CYCLOHEXASILOXANE•PHENYL
TRIMETHICONE•GLYCERIN•BUTYLENE GLYCOL DICAPRYLATE/
DICAPRATE•DIMETHICONE•BUTYLENE GLYCOL•PEG-8•
NIACINAMIDE•CETYL PEG/PPG-10/1 DIMETHICONE•PENTYLENE
GLYCOL•SODIUM CHLORIDE•DICAPRYLYL CARBONATE•
SORBITAN ISOSTEARATE•DISTEARDIMONIUM HECTORITE•
C30-45 ALKYLDIMETHYLSILYL POLYPROPYLSILSESQUIOXANE•
PHENOXYETHANOL•DIMETHICONE CROSSPOLYMER•
TRIETHOXYCAPRYLYLSILANE•ALUMINUM HYDROXIDE•STEARIC
ACID•ETHYLHEXYLGLYCERIN•ADENOSINE•DISODIUM EDTA•
VITIS VINIFERA (GRAPE) FRUIT EXTRACT•OENOTHERA BIENNIS
(EVENING PRIMROSE) OIL•ONSEN-SUI•SODIUM PCA•UREA•
POLYPERFLUOROMETHYLISOPROPYL ETHER•LONICERA
JAPONICA (HONEYSUCKLE) FLOWER EXTRACT•IMPERATA
CYLINDRICA ROOT EXTRACT•TREHALOSE•POLYQUATERNIUM-51•
CITRUS RETICULATA (TANGERINE) PEEL EXTRACT•
ACHYRANTHES FAURIEI ROOT EXTRACT•SODIUM
HYALURONATE•TRIACETIN•CAPRYLYL GLYCOL•1,2-HEXANEDIOL•
CARBOMER•METHYLPARABEN•POTASSIUM SORBATE•OXYGEN•
BUTYLPARABEN•ETHYLPARABEN•PROPYLPARABEN•
ISOBUTYLPARABEN•FRAGRANCE(PARFUM)•
MICA (CI 77019)•IRON OXIDES (CI 77491,
CI 77492, CI 77499)

Other Information

Protect the product in this container from excessive heat and
direct sun.
May stain or damage some fabrics or surfaces.

Questions or comments? Call 1 (866) 638-8417

Distributed by:

THEFACESHOP NORTH AMERICA, INC.
Santa Fe Springs, CA 90670

PACKAGE LABEL

COLOR CONTROL

CC

CREAM

PURE CC

SUNSCREEN CREAM SPF30

02 NATURAL BEIGE